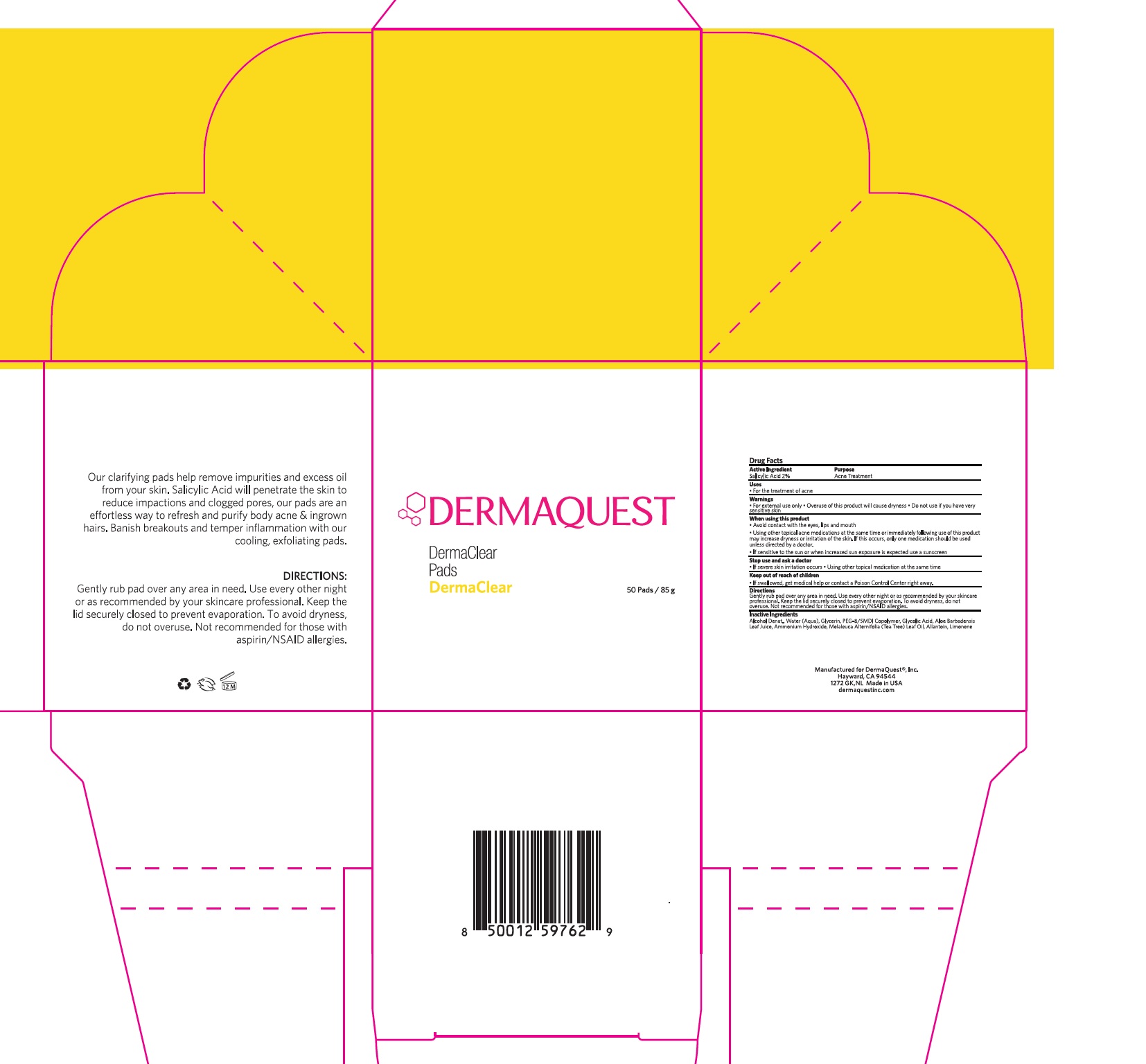 DRUG LABEL: DermaClear Pads
NDC: 62742-4076 | Form: LIQUID
Manufacturer: Allure Labs
Category: otc | Type: HUMAN OTC DRUG LABEL
Date: 20241205

ACTIVE INGREDIENTS: SALICYLIC ACID 20 mg/1 g
INACTIVE INGREDIENTS: ALCOHOL; GLYCERIN; ALOE VERA LEAF; WATER; PEG-8/SMDI COPOLYMER; GLYCOLIC ACID; LIMONENE, (+)-; AMMONIA; TEA TREE OIL; ALLANTOIN

Drug Facts

Active Ingredient - Salicylic Acid 2%

Purpose: Acne Treatment

INDICATIONS AND USAGE

Uses: For treatment of Acne

Warnings:

- For external use only.
- Overuse of this product will cause dryness.

Do not use if you have sensitive skin.

When using this product:

- Avoid contact with the eyes, lips and mouth.
- Using other topical acne medications at the same time or immediately following use of this product may increase dryness or irritation of the skin. If this occurs, only one medication should be used unless directed by a doctor.
- If sensitive to the sun or when increased sun exposure is expected, use a sunscreen.

Stop use and ask a doctor:

- If severe skin irritation occurs.
- When using other topical medication at the same time.

Keep out of reach of children:

- If swallowed, get medical help or contact a Poison Control Center right away.

DOSAGE AND ADMINISTRATION

Gently rub pad over any area in need. Use every other night or as recommended by your skin care prifessional. Keep the lid securely closed to prevent evapration. To avoid dryness, do not overuse. Not recommended for those with aspirin / NASID allergies.

Inactive Ingredients:

Alcohol Denat., Water (Aqua), Glycerin, PEG-8/SMDI Copolymer, Glycolic Acid, Aloe Barbadensis Leaf Juice, Ammonium Hydroxide, Melaleuca Alternifolia Leaf Oil, Allantoin, Limonene.

PACKAGE LABEL

Manufactured for DermaQuest®, Inc.

Hayward, CA 94544

1272 GK, NL Made in USA

dermaquestinc.com